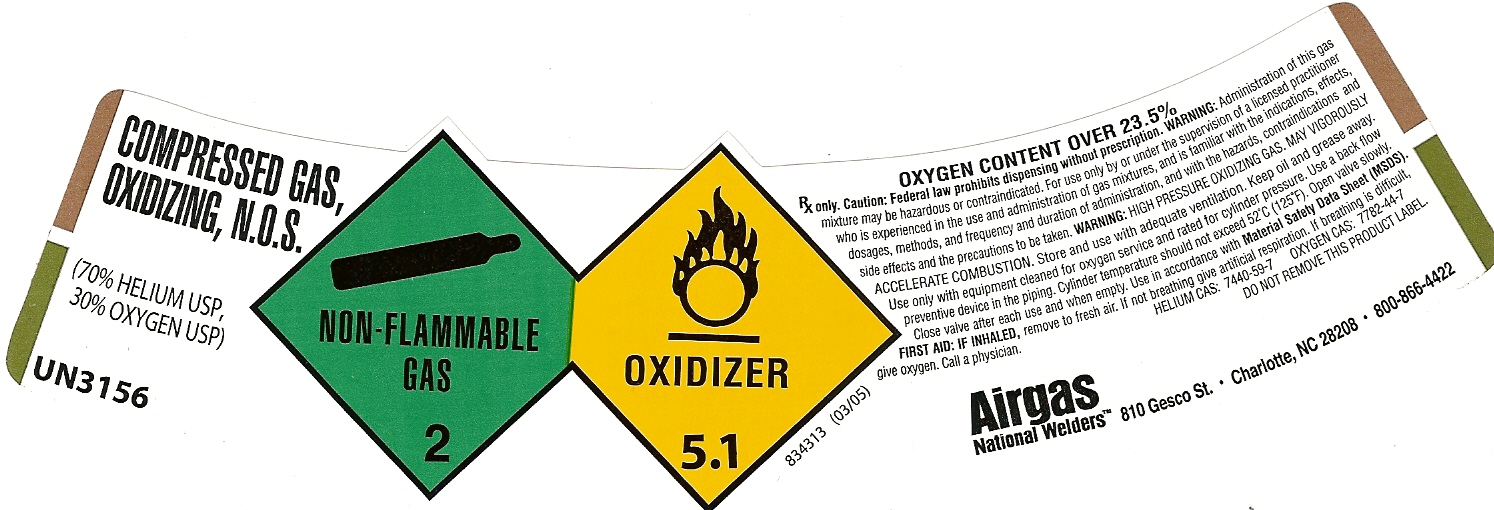 DRUG LABEL: Helium Oxygen
NDC: 11896-0018 | Form: GAS
Manufacturer: Airgas National Welders
Category: prescription | Type: HUMAN PRESCRIPTION DRUG LABEL
Date: 20101018

ACTIVE INGREDIENTS: Helium 700 mL/1 L; Oxygen 300 mL/1 L

HELIUM OXYGEN LABEL 70 30

PACKAGE LABEL

COMPRESSED GAS,OXIDIZING,N.O.S. (70% HELIUM USP,30% OXYGEN USP)UN3156 NON-FLAMMABLE GAS 2 OXIDIZER 5.1 834313 (03/05) OXYGEN CONTENT OVER 23.5% RX ONLY.CAUTION:FEDERAL LAW PROHIBITS DISPENSING WITHOUT PRESCRIPTION.WARNING:ADMINISTRATION OF THIS GAS MIXTURE MAY BE HAZARDOUS OR CONTRAINDICATED.FOR USE ONLY BY OR UNDER THE SUPERVISION OF A LICENSED PRACTITIONER WHO IS EXPERIENCED IN THE USE AND ADMINISTRATION OF GAS MIXTURES, AND IS FAMILIAR WITH THE INDICATIONS , EFFECTS, DOSAGES, METHODS, AND FREQUENCY AND DURATION OF ADMINISTRATION, AND WITH THE HAZARDS, CONTRAINDICATIONS AND SIDE EFFECTS AND THE PRECAUTIONS TO BE TAKEN.WARNING:HIGH PRESSURE OXIDIZING GAS. MAY VIGOROUSLY ACCELERATE COMBUSTION. STORE AND USE WITH ADEQUATE VENTILATION. KEEP OIL AND GREASE AWAY. USE ONLY WITH EQUIPMENT CLEANED FOR OXYGEN SERVICE AND RATED FOR CYLINDER PRESSURE. USE A BACK FLOW PREVENTIVE DEVICE IN THE PIPING. CYLINDER TEMPERATURE SHOULD NOT EXCEED 52'C (125'F). OPEN VALVE SLOWLY. CLOSE VALVE AFTER EACH USE AND WHEN EMPTY. USE IN ACCORDANCE WITH MATERIAL SAFETY DATA SHEET (MSDS). FIRST AID: IF INHALED, REMOVE TO FRESH AIR. IF NOT BREATHING GIVE ARTIFICIAL RESPIRATION. IF BREATHING IS DIFFICULT, GIVE OXYGEN. CALL A PHYSICIAN. HELIUM CAS:7440-59-7 OXYGEN CAS:7782-44-7 DO NOT REMOVE THIS LABEL. AIRGAS NATIONAL WELDERS 810 GESCO ST.* CHARLOTTE, NC 28208* 800-866-4422